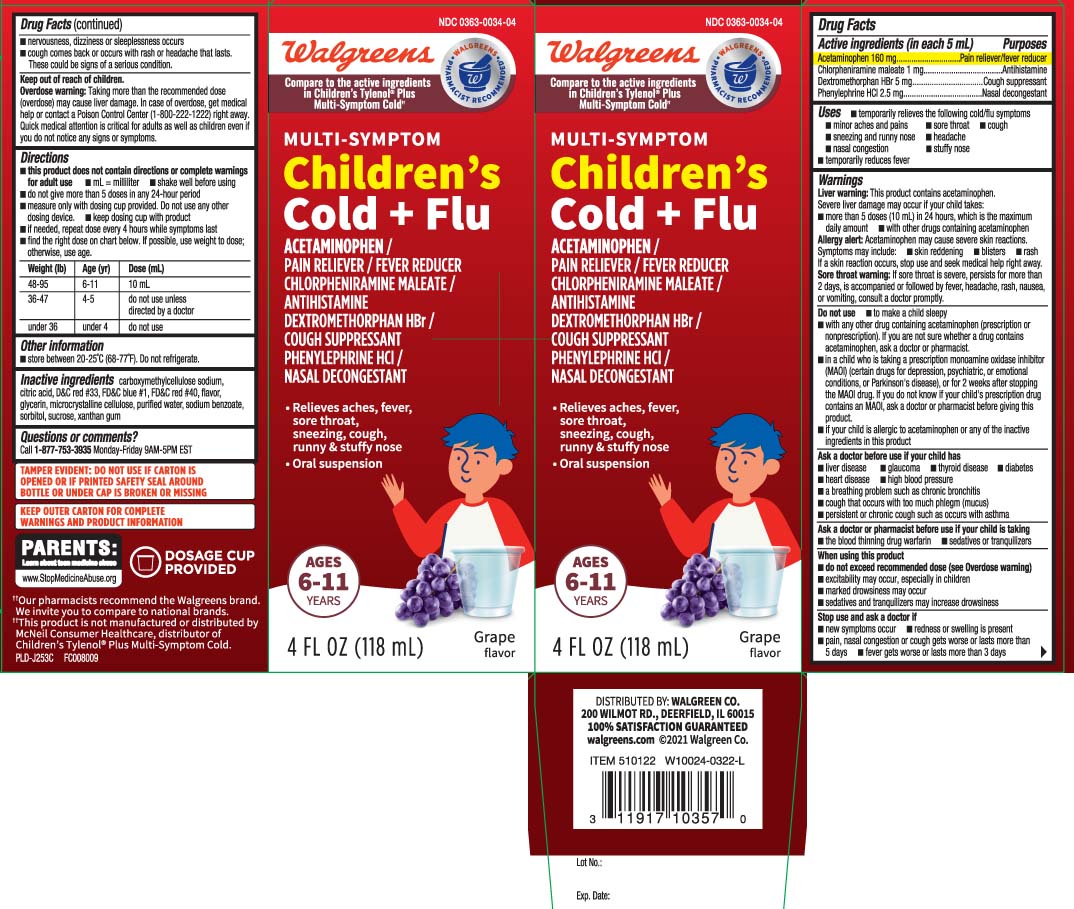 DRUG LABEL: Childrens Plus Multi Symptom Cold
NDC: 0363-0034 | Form: SUSPENSION
Manufacturer: Walgreens
Category: otc | Type: HUMAN OTC DRUG LABEL
Date: 20240508

ACTIVE INGREDIENTS: ACETAMINOPHEN 160 mg/5 mL; CHLORPHENIRAMINE MALEATE 1 mg/5 mL; DEXTROMETHORPHAN HYDROBROMIDE 5 mg/5 mL; PHENYLEPHRINE HYDROCHLORIDE 2.5 mg/5 mL
INACTIVE INGREDIENTS: CARBOXYMETHYLCELLULOSE SODIUM; CELLULOSE, MICROCRYSTALLINE; ANHYDROUS CITRIC ACID; D&C RED NO. 33; FD&C BLUE NO. 1; FD&C RED NO. 40; GLYCERIN; WATER; SODIUM BENZOATE; SORBITOL; SUCROSE; XANTHAN GUM

Drug Facts

Active ingredients (in each 5 mL)

Acetaminophen 160 mg

Chlorpheniramine maleate 1 mg

Dextromethorphan HBr 5 mg

Phenylephrine HCl 2.5 mg

Purposes

Pain reliever/fever reducer

Antihistamine

Cough suppressant

Nasal decongestant

Uses

- temporarily relieves the following cold/flu symptoms:
  - minor aches and pains
  - sore throat
  - cough
  - sneezing and runny nose
  - headache
  - nasal congestion
  - stuffy nose
- temporarily reduces fever

Warnings

Liver warning: This product contains acetaminophen. Severe liver damage may occur if your child takes:

- more than 5 doses (10 mL) in 24 hours, which is the maximum daily amount
- with other drugs containing acetaminophen

Allergy alert: Acetaminophen may cause severe skin reactions. Symptoms may include:

- skin reddening
- blisters
- rash

If a skin reaction occurs, stop use and seek medical help right away.

Sore throat warning: If sore throat is severe, persists for more than 2 days, is accompanied or followed by fever, headache, rash, nausea, or vomiting, consult a doctor promptly.

Do not use

- to make a child sleepy
- in a child who is taking a prescription monoamine oxidase inhibitor (MAOI) (certain drugs for depression, psychiatric or emotional conditions, or Parkinson’s disease), or for 2 weeks after stopping the MAOI drug. If you do not know if your child's prescription drug contains an MAOI, ask a doctor or pharmacist before giving this product.
- with any other drug containing acetaminophen (prescription or non-prescription). If you are not sure whether a drug contains acetaminophen, ask a doctor or pharmacist.
- if your child is allergic to acetaminophen or any of the inactive ingredients in this product

Ask a doctor before use if the child has

- liver disease
- glaucoma
- thyroid disease
- diabetes
- heart disease
- high blood pressure
- a breathing problem such as chronic bronchitis
- persistent or chronic cough such as occurs with asthma
- cough that occurs with too much phlegm (mucus)

Ask a doctor or pharmacist before use if your child is taking

- sedatives or tranquilizers
- the blood thinning drug warfarin

When using this product

- do not exceed recommended dose (see overdose warning)
- excitability may occur, especially in children
- marked drowsiness may occur
- sedatives and tranquilizers may increase drowsiness

Stop use and ask a doctor if

- new symptoms occur
- redness or swelling is present
- pain, nasal congestion or cough gets worse or lasts more than 5 days
- fever gets worse or lasts more than 3 days
- nervousness, dizziness or sleeplessness occurs
- cough comes back or occurs with rash or headache that lasts.These could be signs of a serious condition.

Keep out of reach of children.

Overdose warning: Taking more than the recommended dose (overdose) may cause liver damage. In case of overdose, get medical help or contact a Poison Control Center (1-800-222-1222) right away. Quick medical attention is critical even if you do not notice any signs or symptoms.

Directions

- this product does not contain directions or complete warnings for adult use
- mL=milliliter
- shake well before using
- do not give more than 5 doses in any 24-hour peroid
- measure only with dosing cup provided. Do not use any other dosing device.
- keep dosing cup with product
- if needed, repeat dose every 4 hours while symptoms last
- find the right dose on chart below. If possible, use weight to dose, otherwise, use age.

Weight (lb) | Age (yr) | Dose (mL)
48-95 | 6-11 | 10 mL
36-47 | 4-5 | do not use unless directed by a doctor
under 36 | under 4 | do not use

Other Information

- store between 20-25ºC (68-77ºF). Do not refrigerate

Inactive ingredients

anhydrous citric acid, carboxymethylcellulose sodium, D&C red #33, FD&C blue #1, FD&C red #40, flavor, glycerin, microcrystalline cellulose, purified water, sodium benzoate, sorbitol, sucrose, xanthan gum

Questions or comments?

Call 1-877-753-3935 Monday-Friday 9AM-5PM EST

Principal Display Panel

Compare to the active ingredients in Children's Tylenol® Plus Multi-Symptom Cold††

Multi-Symptom

Children's

Cold + Flu

ACETAMINOPHEN /

PAIN RELIEVER / FEVER REDUCER

CHLORPHENIRAMINE MALEATE /

ANTIHISTAMINE

DEXTROMETHORPHAN HBr /

COUGH SUPPRESSANT

PHENYLEPHRINE HCI /

NASAL DECONGESTANT

- Relieves aches, fever, sore throat, sneezing, cough, runny & stuffy nose
- Oral suspension

AGES 6 -11 YEARS

FL OZ (mL)

Grape flavor

DOSAGE CUP PROVIDED

††This product is not manufactured or distributed bt McNeil Consumer Healthcare, distributor of Children's Tylenol® Plus Multi-Symptom Cold.

TAMPER EVIDENT: DO NOT USE IF CARTON IS OPENED OR IF PRINTED SAFETY SEAL AROUND BOTTLE OR UNDER CAP IS BROKEN OR MISSING.

KEEP OUTER CARTON FOR COMPLETE WARNINGS AND PRODUCT INFORMATION

DISTRIBUTED BY: WALGREEN CO

200 WILMOT RD., DEERFIELD, IL 60015

walgreens.com

Package Label

WALGREENS Multi-Symptom Children's Cold and Flu